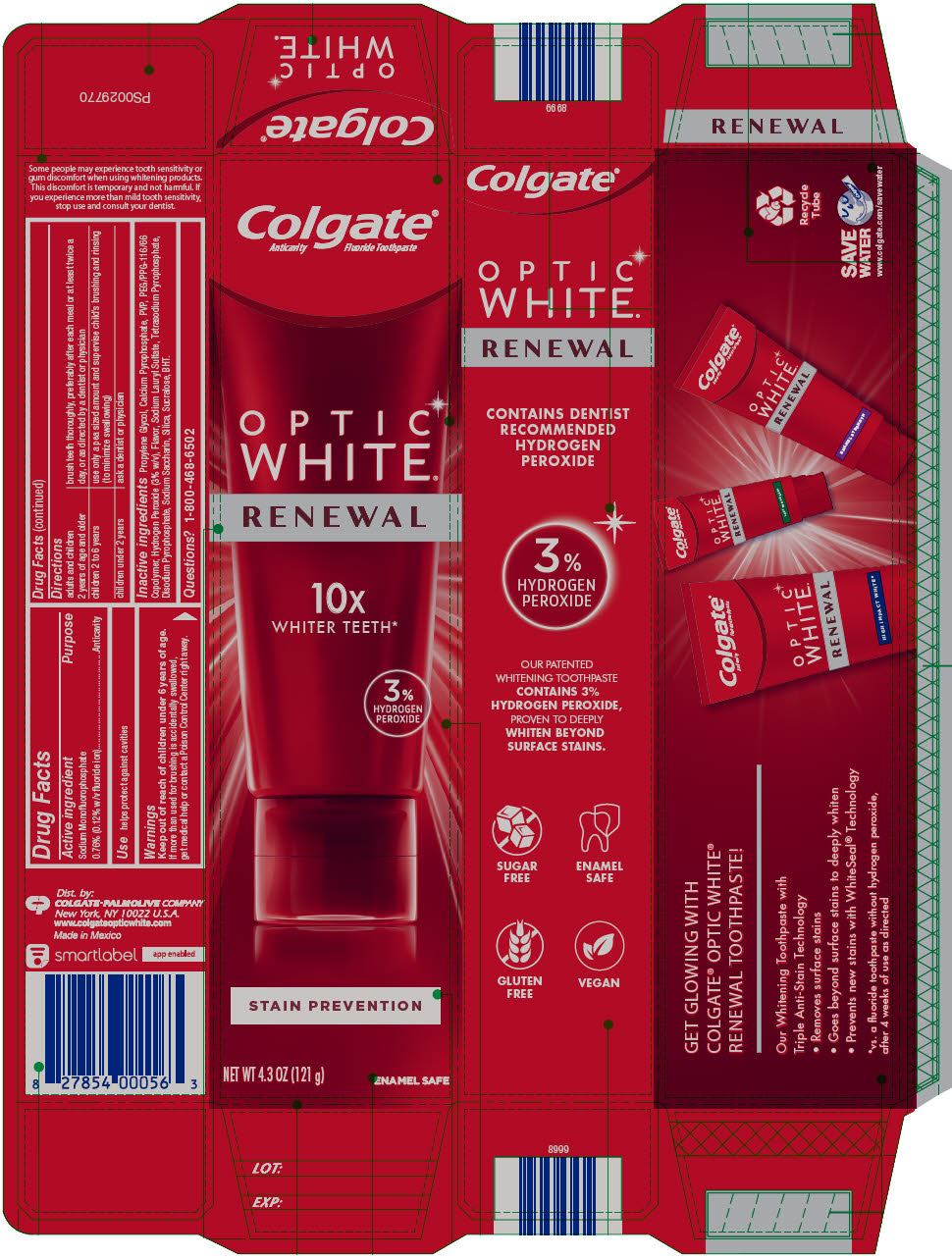 DRUG LABEL: Colgate Optic White Stain Prevention
NDC: 35000-893 | Form: PASTE, DENTIFRICE
Manufacturer: Colgate-Palmolive Company
Category: otc | Type: HUMAN OTC DRUG LABEL
Date: 20241017

ACTIVE INGREDIENTS: SODIUM MONOFLUOROPHOSPHATE 1 mg/1 g
INACTIVE INGREDIENTS: PROPYLENE GLYCOL 527 mg/1 g; CALCIUM PYROPHOSPHATE; POVIDONE K15; PEG/PPG-116/66 COPOLYMER; HYDROGEN PEROXIDE; SODIUM LAURYL SULFATE; SODIUM PYROPHOSPHATE; SACCHARIN SODIUM; SODIUM ACID PYROPHOSPHATE; SILICON DIOXIDE; SUCRALOSE; BUTYLATED HYDROXYTOLUENE

Colgate® Optic White® Stain Prevention

Drug Facts

Active ingredient

Sodium Monofluorophosphate 0.76% (0.12% w/v fluoride ion)

Purpose

Anticavity

Use

helps protect against cavities

Warnings

Keep out of reach of children under 6 years of age. If more than used for brushing is accidentally swallowed, get medical help or contact a Poison Control Center right away.

Directions

adults and children 2 years of age and older | brush teeth thoroughly, preferably after each meal or at least twice a day, or as directed by a dentist or physician
children 2 to 6 years | use only a pea sized amount and supervise child's brushing and rinsing (to minimize swallowing)
children under 2 years | ask a dentist or physician

Inactive ingredients

Propylene Glycol, Calcium Pyrophosphate, PVP, PEG/PPG-116/66 Copolymer, Hydrogen Peroxide (3% w/v), Flavor, Sodium Lauryl Sulfate, Tetrasodium Pyrophosphate, Disodium Pyrophosphate, Sodium Saccharin, Silica, Sucralose, BHT.

Questions?

1-800-468-6502

Dist. by:
COLGATE-PALMOLIVE COMPANY
New York, NY 10022 U.S.A.

PRINCIPAL DISPLAY PANEL - 121 g Tube Carton

Colgate®
Anticavity Fluoride Toothpaste

OPTIC
WHITE®
RENEWAL

10x
WHITER TEETH*

3%
HYDROGEN
PEROXIDE

STAIN PREVENTION

NET WT 4.3 OZ (121 g)
ENAMEL SAFE